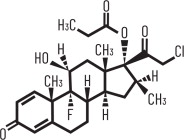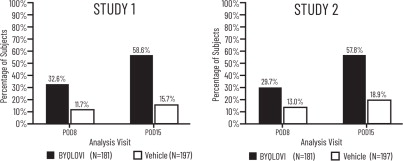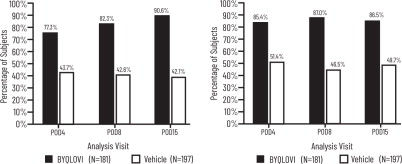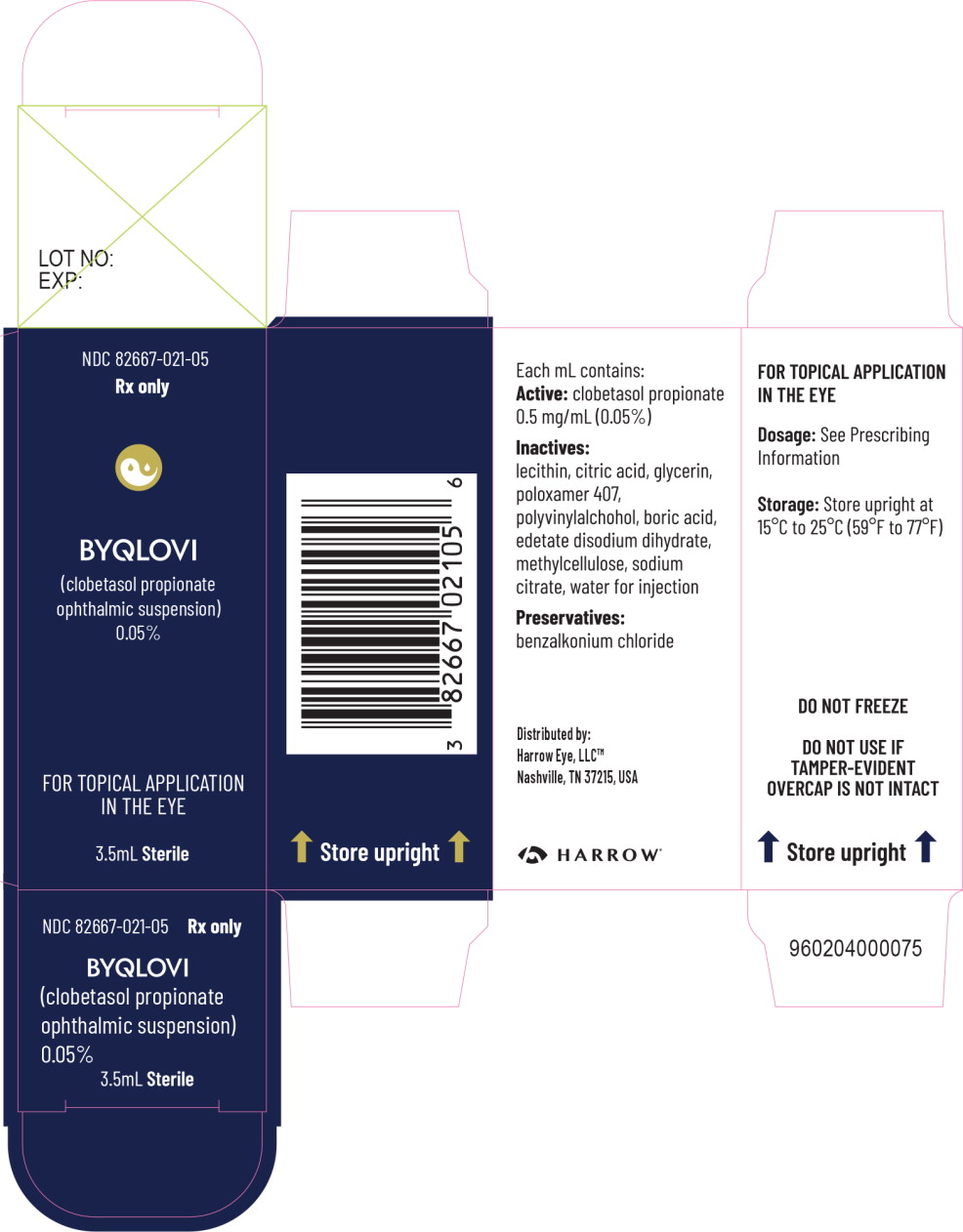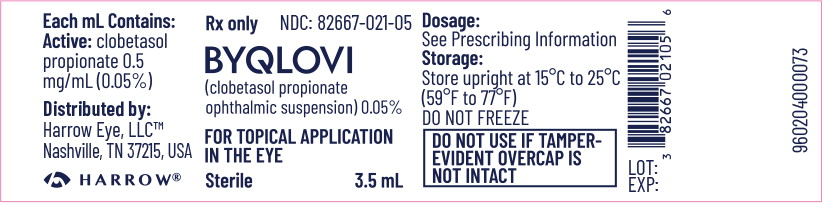 DRUG LABEL: BYQLOVI
NDC: 82667-021 | Form: FOR SUSPENSION
Manufacturer: Harrow Eye, LLC
Category: prescription | Type: HUMAN PRESCRIPTION DRUG LABEL
Date: 20260126

ACTIVE INGREDIENTS: CLOBETASOL PROPIONATE 0.5 mg/1 mL
INACTIVE INGREDIENTS: SODIUM CHLORIDE; HYDROGENATED SOYBEAN LECITHIN; CITRIC ACID MONOHYDRATE; GLYCERIN; POLOXAMER 407; POLYVINYL ALCOHOL, UNSPECIFIED; BORIC ACID; EDETATE DISODIUM; METHYLCELLULOSE, UNSPECIFIED; ANHYDROUS TRISODIUM CITRATE; WATER

HIGHLIGHTS OF PRESCRIBING INFORMATION

These highlights do not include all the information needed to use BYQLOVI®safely and effectively. See full prescribing information for BYQLOVI.
BYQLOVI (clobetasol propionate ophthalmic suspension) 0.05%, for topical ophthalmic use
Initial U.S. Approval: 1985

1 INDICATIONS AND USAGE

BYQLOVI is a corticosteroid indicated for the treatment of post- operative inflammation and pain following ocular surgery. (1)

2 DOSAGE AND ADMINISTRATION

- Instill one drop of BYQLOVI into the affected eye twice daily beginning the day after surgery and continuing throughout the first 2 weeks of the post-operative period. (2.1)
- Wash hands well before each use. (2.2)

3 DOSAGE FORMS AND STRENGTHS

Ophthalmic suspension containing clobetasol propionate 0.05%. (3)

4 CONTRAINDICATIONS

BYQLOVI is contraindicated in most active viral diseases of the cornea and conjunctiva, including epithelial herpes simplex keratitis (dendritic keratitis), vaccinia, and varicella, and also in mycobacterial infection of the eye and fungal diseases of ocular structures. (4)

5 WARNINGS AND PRECAUTIONS

- Intraocular Pressure (IOP) Increase: Prolonged use of corticosteroids may result in glaucoma with damage to the optic nerve, defects in visual acuity and fields of vision. Steroids should be used with caution in the presence of glaucoma. If this product is used for 10 days or longer, IOP should be monitored. (5.1)
- Cataracts: Prolonged use of corticosteroids may result in posterior subcapsular cataract formation. (5.2)
- Delayed Healing: The use of steroids after cataract surgery may delay healing and increase the incidence of bleb formation. (5.3)
- Corneal and Scleral Melting: In those diseases causing thinning of the cornea or sclera, perforations have been known to occur with the use of topical steroids. The initial prescription and renewal of the medication order should be made by a physician only after examination of the patient with the aid of magnification, such as slit lamp biomicroscopy, and where appropriate, fluorescein staining. (5.4)
- Bacterial Infections: Prolonged use of corticosteroids may suppress the host response and thus increase the hazard of secondary ocular infections. In acute purulent conditions, steroids may mask infection or enhance existing infection. If signs and symptoms fail to improve after 2 days, the patient should be reevaluated. (5.5)
- Viral Infections: Employment of a corticosteroid medication in the treatment of patients with a history of herpes simplex requires great caution. Use of ocular steroids may prolong the course and may exacerbate the severity of many viral infections of the eye (including herpes simplex). (5.6)
- Fungal Infections: Fungal infections of the cornea are particularly prone to develop coincidentally with long-term local steroid application. Fungus invasion must be considered in any persistent corneal ulceration where a steroid has been used or is in use. Fungal culture should be taken when appropriate. (5.7)

6 ADVERSE REACTIONS

Ocular adverse reactions occurring in ≥ 1% of subjects in clinical studies who received BYQLOVI included eye inflammation (2%), corneal edema (2%), anterior chamber inflammation (2%), cystoid macular edema (2%), intraocular pressure elevation (1%), photophobia (1%) and vitreous detachment (1%). Many of these reactions may have been the consequence of the surgical procedure (6.1).

To report SUSPECTED ADVERSE REACTIONS, contact Harrow at 1-833-4HARROW(427769) or FDA at 1-800-FDA-1088 orwww.fda.gov/medwatch.

FULL PRESCRIBING INFORMATION

1 INDICATIONS AND USAGE

BYQLOVI is indicated for the treatment of post-operative inflammation and pain following ocular surgery.

2 DOSAGE AND ADMINISTRATION

2.1 Recommended Dosage

Instill one drop of BYQLOVI into the affected eye twice daily beginning the day after surgery and continuing throughout the first 2 weeks of the post-operative period.

2.2 Administration Instructions

Wash hands well before each use.

If using other eye drops in addition to BYQLOVI, wait at least 5 minutes between instillation of BYQLOVI and other eye drops.

3 DOSAGE FORMS AND STRENGTHS

Ophthalmic suspension containing clobetasol propionate 0.05% (0.5 mg/mL).

4 CONTRAINDICATIONS

BYQLOVI is contraindicated in most active viral diseases of the cornea and conjunctiva, including epithelial herpes simplex keratitis (dendritic keratitis), vaccinia, and varicella, and also in mycobacterial infection of the eye and fungal diseases of ocular structures.

5 WARNINGS AND PRECAUTIONS

5.1 Intraocular Pressure (IOP) Increase

Prolonged use of corticosteroids may result in glaucoma with damage to the optic nerve, defects in visual acuity and fields of vision. Steroids should be used with caution in the presence of glaucoma. If BYQLOVI is used for 10 days or longer, IOP should be monitored.

5.2 Cataracts

Prolonged use of corticosteroids may result in posterior subcapsular cataract formation.

5.3 Delayed Healing

The use of corticosteroids after cataract surgery may delay healing and increase the incidence of bleb formation.

5.4 Corneal and Scleral Melting

In those diseases causing thinning of the cornea or sclera, perforations have been known to occur with the use of topical corticosteroids. The initial prescription and renewal of the medication order should be made by a physician only after examination of the patient with the aid of magnification, such as slit lamp biomicroscopy, and where appropriate, fluorescein staining.

5.5 Bacterial Infections

Prolonged use of corticosteroids may suppress the host response and thus increase the hazard of secondary ocular infections. In acute purulent conditions, steroids may mask infection or enhance existing infection. If signs and symptoms fail to improve after 2 days, the patient should be reevaluated.

5.6 Viral Infections

Employment of a corticosteroid medication in the treatment of patients with a history of herpes simplex requires great caution. Use of ocular corticosteroids may prolong the course and may exacerbate the severity of many viral infections of the eye (including herpes simplex).

5.7 Fungal Infections

Fungal infections of the cornea are particularly prone to develop coincidentally with long- term local corticosteroid application. Fungus invasion must be considered in any persistent corneal ulceration where a corticosteroid has been used or is in use. Fungal culture should be taken when appropriate.

5.8 Risk of Contamination

Do not allow the dropper tip to touch any surface, as this may contaminate the ophthalmic suspension.

5.9 Contact Lens Wear

BYQLOVI should not be instilled while wearing contact lenses. Remove contact lenses prior to instillation of BYQLOVI. The preservative in BYQLOVI may be absorbed by soft contact lenses. Lenses may be reinserted after 15 minutes following administration of BYQLOVI.

6 ADVERSE REACTIONS

The following serious reactions are found elsewhere in the labeling:

- Intraocular Pressure (IOP) Increase [see Warnings and Precautions (5.1)]
- Posterior Subcapsular Cataract Formation [see Warnings and Precautions (5.2)]
- Delayed Healing [see Warnings and Precautions (5.3)]
- Corneal and Scleral Melting [see Warnings and Precautions (5.4)]
- Bacterial Infections [see Warnings and Precautions (5.5)]
- Viral Infections [see Warnings and Precautions (5.6)]
- Fungal Infections [see Warnings and Precautions (5.7)]

6.1 Clinical Trials Experience

Because clinical trials are conducted under widely varying conditions, adverse reaction rates observed in the clinical trials of a drug cannot be directly compared to rates in the clinical trials of another drug and may not reflect the rates observed in practice.

Ocular adverse reactions occurring in ≥ 1% of subjects in clinical studies who received BYQLOVI included eye inflammation (2%), corneal edema (2%), anterior chamber inflammation (2%), cystoid macular edema (2%), intraocular pressure elevation (1%), photophobia (1%) and vitreous detachment (1%). Many of these reactions may have been the consequence of the surgical procedure.

8 USE IN SPECIFIC POPULATIONS

8.1 Pregnancy

Risk Summary

There are no adequate and well-controlled clinical studies of BYQLOVI administration in pregnant women to inform drug-associated risks. Plasma concentrations of clobetasol propionate were minimal following topical ophthalmic administration of BYQLOVI [see Clinical Pharmacology (12.3)] . However, corticosteroids, including clobetasol propionate have been shown to be teratogenic and fetotoxic in laboratory animals when administered systemically at relatively low dosage levels (see Data) .

BYQLOVI should be used during pregnancy only if the potential benefit justifies the potential risk to the fetus.

In the US general population, the estimated background risk of major birth defects and miscarriage in clinically recognized pregnancies is 2-4% and 15-20%, respectively.

Data

Animal Data

In embryofetal development studies in mice, clobetasol propionate was fetotoxic at the highest subcutaneous dose tested (1 mg/kg) and teratogenic at all subcutaneous dose levels tested down to 0.03 mg/kg. Abnormalities observed included cleft palate and skeletal abnormalities. These doses are approximately 98 times and 3 times, respectively, the recommended human ophthalmic dose of BYQLOVI, estimated based on body surface area and assuming 100% systemic absorption.

In embryofetal development studies in rabbits, clobetasol propionate was teratogenic at subcutaneous doses of 3 and 10 μg/kg. Abnormalities seen included cleft palate, cranioschisis, and other skeletal abnormalities. These doses are approximately 1.2 times and 3.9 times, respectively, the recommended human ophthalmic dose of BYQLOVI, estimated based on body surface area and assuming 100% systemic absorption.

8.2 Lactation

Risk Summary

There is no information regarding the presence of clobetasol propionate in human milk, the effects on the breastfed infant, or the effects on milk production.

Systemically administered corticosteroids appear in human milk and could suppress growth, interfere with endogenous corticosteroid production, or cause other untoward effects. However, systemic levels of clobetasol propionate following topical ocular administration are minimal [see Clinical Pharmacology (12.3)], and it is not known whether measurable levels of clobetasol propionate would be present in maternal milk following topical ocular administration.

The developmental and health benefits of breastfeeding should be considered along with the mother's clinical need for BYQLOVI, and any potential adverse effects on the breastfed infant from BYQLOVI.

8.4 Pediatric Use

The safety and effectiveness of BYQLOVI in pediatric patients have not been established.

8.5 Geriatric Use

No overall differences in safety and effectiveness of BYQLOVI have been observed between patients 65 years of age and older and younger adult patients.

11 DESCRIPTION

BYQLOVI (clobetasol propionate ophthalmic suspension) 0.05% contains the active compound clobetasol propionate, a synthetic corticosteroid, that has a high degree of glucocorticoid activity and a slight degree of mineralocorticoid activity.

Chemically, clobetasol propionate is 21-chloro-9-fluoro-11β,17-dihydroxy-16β- methylpregna- 1,4-diene-3,20-dione 17-propionate and it has the following structural formula:

Clobetasol propionate has the empirical formula C25H32CIFO5 and a molecular weight of 467. BYQLOVI contains a sterile, anti-inflammatory corticosteroid for topical ophthalmic use.

Each mL of BYQLOVI contains:

ACTIVE: clobetasol propionate 0.5 mg (0.05%)

INACTIVES: sodium chloride, hydrogenated soybean lecithin, citric acid, glycerin, poloxamer 407, polyvinyl alcohol, boric acid, edetate disodium dihydrate, methylcellulose, trisodium citrate, and water for injection

PRESERVATIVE: benzalkonium chloride 0.0036%.

12 CLINICAL PHARMACOLOGY

12.1 Mechanism of Action

Like other topical corticosteroids, clobetasol propionate has anti-inflammatory, antipruritic, and vasoconstrictive properties. The mechanism of the anti-inflammatory activity of the topical steroids, in general, is unclear. However, corticosteroids are thought to act by the induction of phospholipase A2 inhibitory proteins, collectively called lipocortins. It is postulated that these proteins control the biosynthesis of potent mediators of inflammation such as prostaglandins and leukotrienes by inhibiting the release of their common precursor, arachidonic acid. Arachidonic acid is released from membrane phospholipids by phospholipase A2.

12.2 Pharmacodynamics

In patients treated with BYQLOVI twice daily for 21 days, the mean (SD) changes from baseline in cortisol concentrations, -18.1 (126.2) nmol/L and +5.1 (129.8) nmol/L for the BYQLOVI and matching vehicle arms, respectively, were not statistically significant, considering the variability observed in the cortisol concentrations.

12.3 Pharmacokinetics

After the first and second (12 hours apart) ocular instillations of BYQLOVI in healthy adults (n=12), peak plasma clobetasol propionate concentrations (Cmax) were below the lower limit of quantitation (LLOQ, 0.04 ng/mL) in 13 out of 22 PK profiles and ranged from 0.040 to 0.182 ng/mL in the other 9 profiles. Time to peak concentration (Tmax) was observed between 0.5 - 1 hour post-dose. Clobetasol propionate concentrations declined to lower than LLOQ after 4 to 5 hours post-dose.

13 NONCLINICAL TOXICOLOGY

13.1 Carcinogenesis, Mutagenesis, Impairment of Fertility

Carcinogenesis

Long-term animal studies have not been performed with BYQLOVI to evaluate the carcinogenic potential of clobetasol propionate.

Mutagenesis

Clobetasol propionate was not mutagenic in 3 different test systems: the Ames test, the Saccharomyces cerevisiae gene conversion assay, and the E. coli B WP2 fluctuation test.

Impairment of Fertility

Fertility studies in the rat following subcutaneous administration at dosage levels up to 50 μg/kg/day revealed that the females exhibited an increase in the number of resorbed embryos and a decrease in the number of living fetuses at the highest dose. This dose is approximately 10 times the recommended human ophthalmic dose of BYQLOVI (0.83 μg/kg/day), estimated based on body surface area and assuming 100% systemic absorption. Note that systemic levels of clobetasol propionate following topical ocular administration are minimal [see Clinical Pharmacology (12.3)].

14 CLINICAL STUDIES

Clinical efficacy was evaluated in 2 multi-center, randomized, double-masked, vehicle- controlled trials in which patients had ≥10 cells in the anterior chamber after cataract surgery were assigned to BYQLOVI 0.05% (N=366) or vehicle (N=382) (NCT04739709 (Study 1) and NCT04810962 (Study 2)). One drop of BYQLOVI 0.05% or vehicle was self-administered twice a day for 14 days, beginning on the day after surgery. Complete resolution of inflammation (an anterior chamber cell count of 0 maintained through Day 15 without rescue medication) and complete resolution of pain (a patient-reported pain grade of 0 maintained through Day 15 without rescue medication) were assessed at post-operative day (POD) 4, 8, and 15.

The co-primary efficacy endpoints were the proportion of subjects with Anterior Chamber Cell (ACC) count = 0 (ACC grade = 0) at POD8 maintained through POD15, and the proportion of subjects with Ocular Pain Grade = 0 at POD4 maintained through POD15. In the intent-to-treat analysis, both co-primary efficacy endpoints were statistically significantly better in BYQLOVI 0.05%-treated patients compared to vehicle- treated patients (p<0.01). The clinical trial efficacy results from both studies are provided below.

Figure 1: Percent of Patients with Anterior Chamber Cell Count = 0 at Post- Operative Days 8 and 15

Figure 2: Percent of Patients with Complete Resolution of Pain at Post-Operative Days 4, 8, and 15

16 HOW SUPPLIED/STORAGE AND HANDLING

16.1 How Supplied

BYQLOVI (clobetasol propionate ophthalmic suspension) 0.05% (0.5 mg/mL) is a sterile ophthalmic suspension. It is supplied in a multi-dose white low- density polyethylene plastic 5 mL eye-dropper bottle with a low-density polyethylene white tip and a high- density polyethylene pink cap with a tamper-proof ring at the bottom of the cap.

3.5 mL in a 5 mL bottle (NDC 82667-021-05)

16.2 Storage and Handling

- Do not use if tamper-evident ring seal is broken.
- Keep the bottle tightly closed with the pink cap when not in use.

Store upright at 15°C to 25°C (59°F to 77°F). Do not freeze. After opening, BYQLOVI can be used until the expiration date on the bottle.

17 PATIENT COUNSELING INFORMATION

Administration with Other Eye Drops

Advise patients to wait at least 5 minutes between instillation of BYQLOVI and other eye drops if using other eye drops in addition to BYQLOVI.

Risk of Contamination

Advise patients to wash their hands well before each use. Advise patients not to allow the dropper tip to touch any surface, as this may contaminate the ophthalmic suspension.

When to Seek Physician Advice

Advise patients to consult a physician if pain develops; or if redness, itching, or inflammation becomes aggravated.

Contact Lens Wear

Advise patients that the preservative in BYQLOVI may be absorbed by soft contact lenses.

Contact lenses should be removed prior to instillation of BYQLOVI and may be reinserted after 15 minutes following administration.

Distributed by:
Harrow Eye, LLC™
Nashville, TN 37215, USA
960204000074
Rev. 09/2025

Principal Display Panel - 3.5 mL Carton Label

NDC 82667-021-05

Rx only

BYQLOVI

(clobetasol propionate
ophthalmic suspension)
0.05%

FOR TOPICAL APPLICATION
IN THE EYE

3.5mL Sterile

Principal Display Panel - 3.5 mL Bottle Label

Rx only NDC: 82667-021-05

BYQLOVI

(clobetasol propionate
ophthalmic suspension) 0.05%

FOR TOPICAL APPLICATION
IN THE EYE

Sterile 3.5 mL